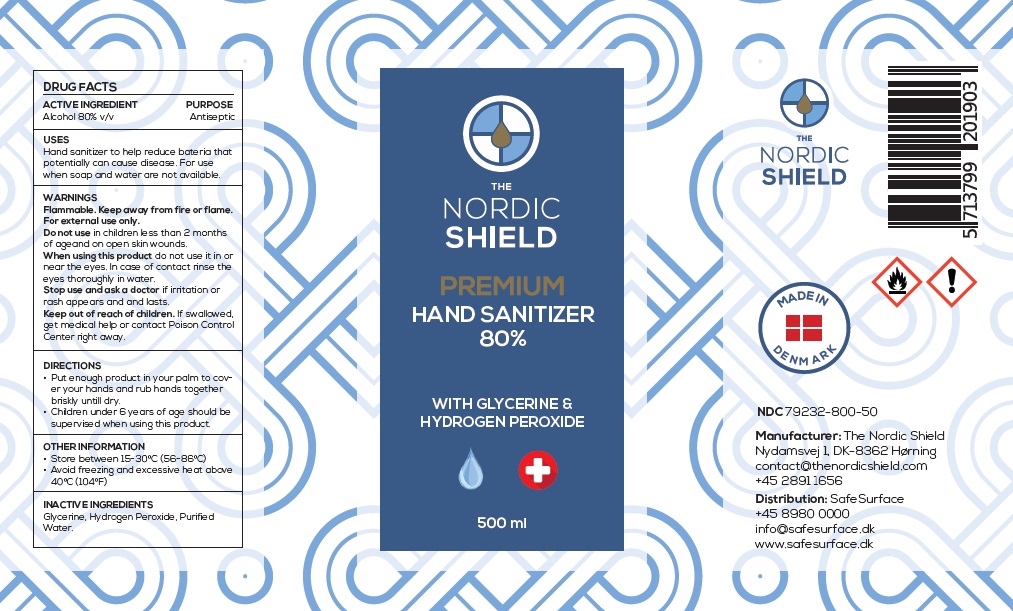 DRUG LABEL: THE NORDIC SHIELD HAND SANITIZER
NDC: 79232-800 | Form: LIQUID
Manufacturer: The Nordic Shield ApS
Category: otc | Type: HUMAN OTC DRUG LABEL
Date: 20200703

ACTIVE INGREDIENTS: ALCOHOL 80 mL/100 mL
INACTIVE INGREDIENTS: GLYCERIN; HYDROGEN PEROXIDE; WATER

THE NORDIC SHIELD PREMIUM HAND SANITIZER

ACTIVE INGREDIENT

Alcohol 80% v/v

PURPOSE

Antiseptic

USES

Hand sanitizer to help reduce bacteria that potentially can cause disease. For use when soap and water are not available.

WARNINGS

Flammable. Keep away from fire or flame.

For external use only.

Do not use in children less than 2 months of age and on open skin wounds.

When using this product do not use it in or near the eyes. In case of contact rinse the eyes thoroughly in water.

Stop use and ask a doctor if irritation or rash appears and lasts.

Keep out of reach of children. If swallowed, get medical help or contact Poison Control Center right away.

DIRECTIONS

• Put enough product in your palm to cover your hands and rub hands together briskly until dry.

• Children under 6 years of age should be supervised when using this product.

OTHER INFORMATION

• Store between 15-30°C (56-86°C)

• Avoid freezing and excessive heat above 40°C (104°F)

INACTIVE INGREDIENTS

Glycerine, Hydrogen Peroxide, Purified Water.

WITH GLYCERINE & HYDROGEN PEROXIDE

MADE IN DENMARK

Manufacturer: The Nordic Shield

Nydamsvej 1, DK-8362 Hørning

contact@thenordicshield.com

+45 2891 1656

Distribution: SafeSurface

+45 8980 0000

info@safesurface.dk

www.safesurface.dk